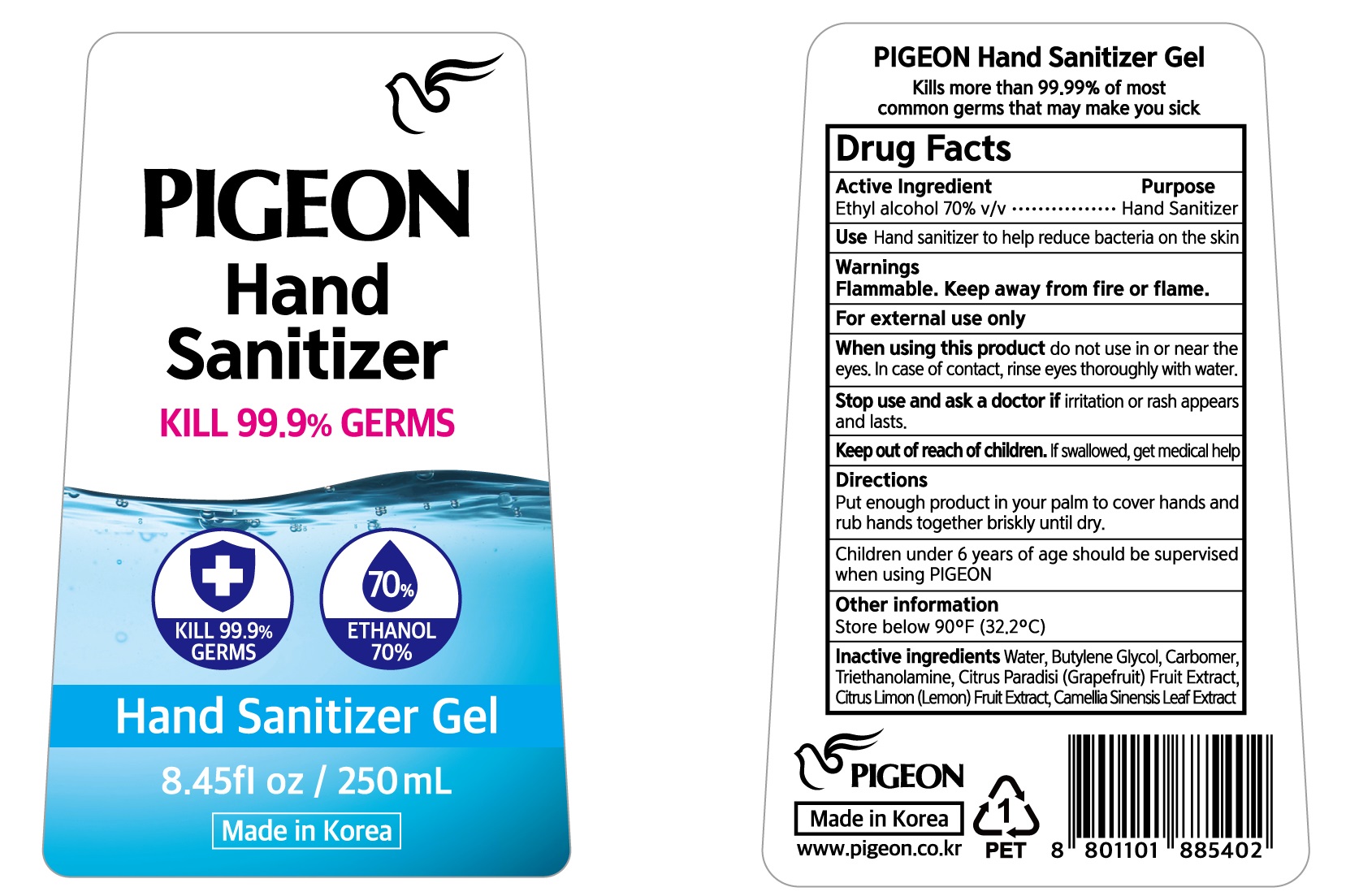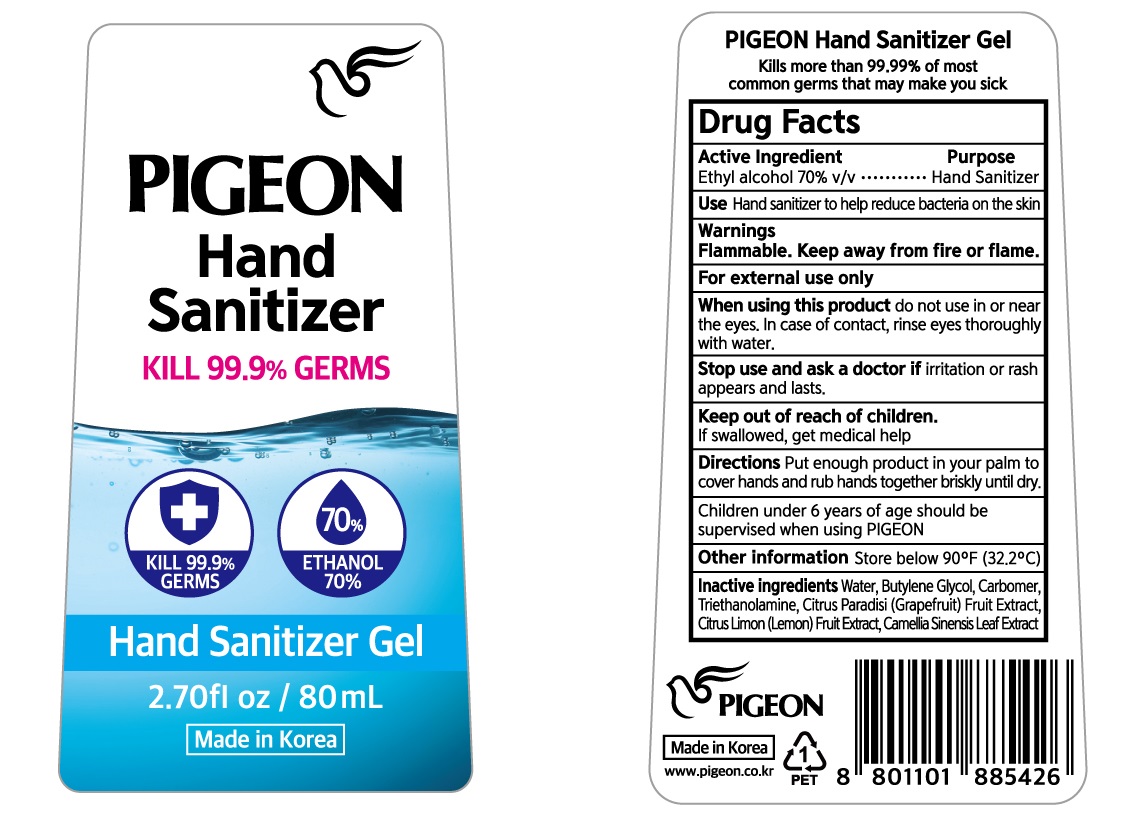 DRUG LABEL: PIGEON Hand Sanitizer
NDC: 78151-010 | Form: GEL
Manufacturer: PIGEON CORPORATION
Category: otc | Type: HUMAN OTC DRUG LABEL
Date: 20200520

ACTIVE INGREDIENTS: ALCOHOL 70 mL/100 mL
INACTIVE INGREDIENTS: Water; Butylene Glycol; CARBOMER HOMOPOLYMER, UNSPECIFIED TYPE; TROLAMINE; GRAPEFRUIT; LEMON; GREEN TEA LEAF

Drug Facts

ACTIVE INGREDIENT

Ethyl Alcohol 70% v/v

INACTIVE INGREDIENT

Water, Butylene Glycol, Carbomer, Triethanolamine, Citrus Paradisi (Grapefruit) Fruit Extract, Citrus Limon (Lemon) Fruit Extract, Camellia Sinensis Leaf Extract

PURPOSE

Hand Sanitizer

WARNINGS

Flammable. Keep away from fire or flame.
For external use only
When using this product do not use in or near the eyes.
In case of contact, rinse eyes thoroughly with water.
Stop use and ask a doctor if irritation or rash appears and lasts.

KEEP OUT OF REACH OF CHILDREN

If swallowed, get medical help

Uses:

Hand sanitizer to help reduce bacteria on the skin

Directions

Put enough product in your palm to cover hands and rub hands together briskly until dry.

Children under 6 years of age should be supervised when using PIGEON

Other information

Store below 90ºF (32.2ºC)